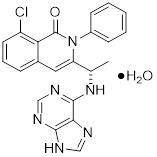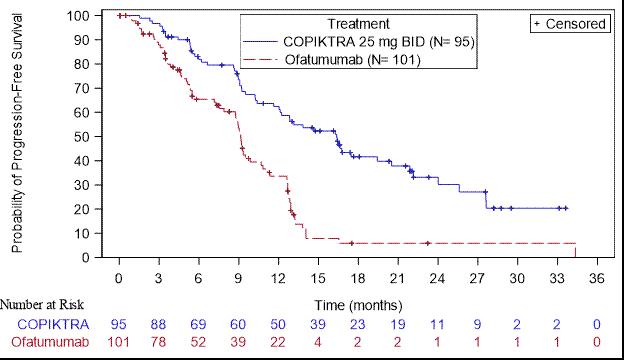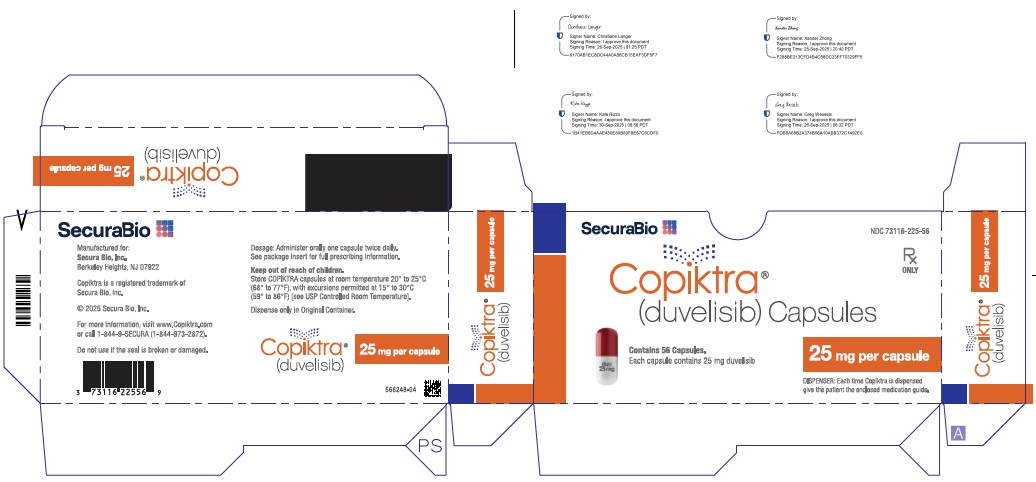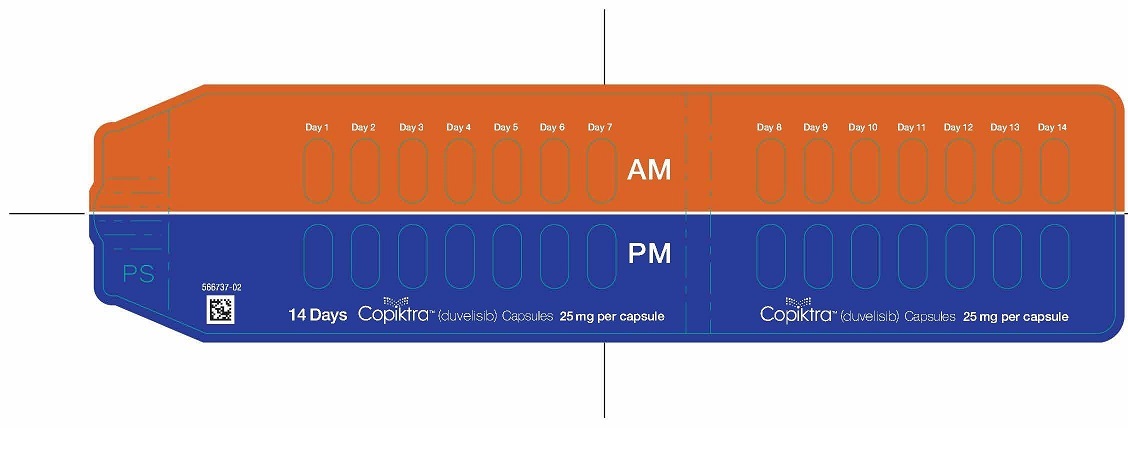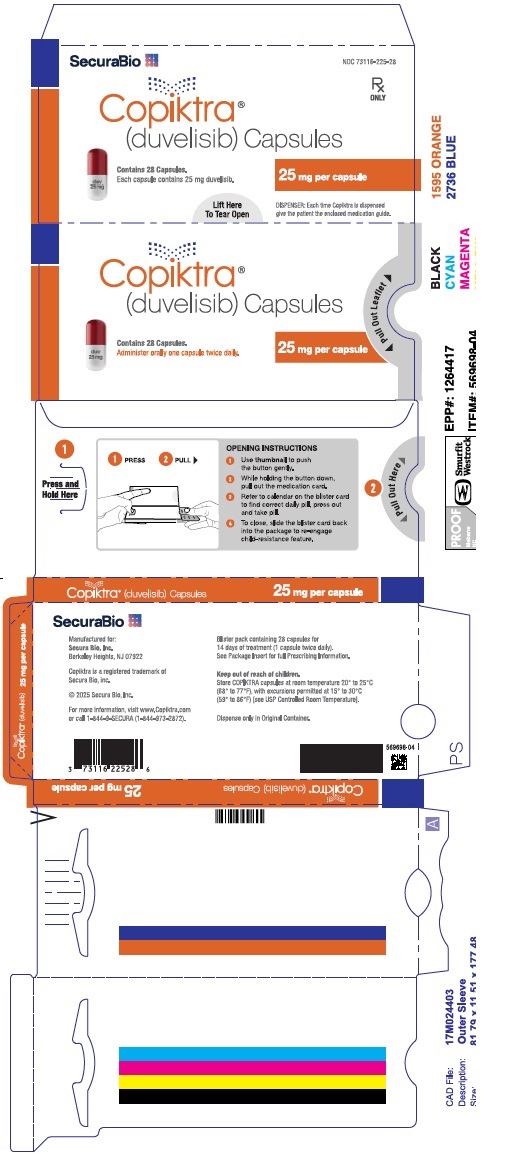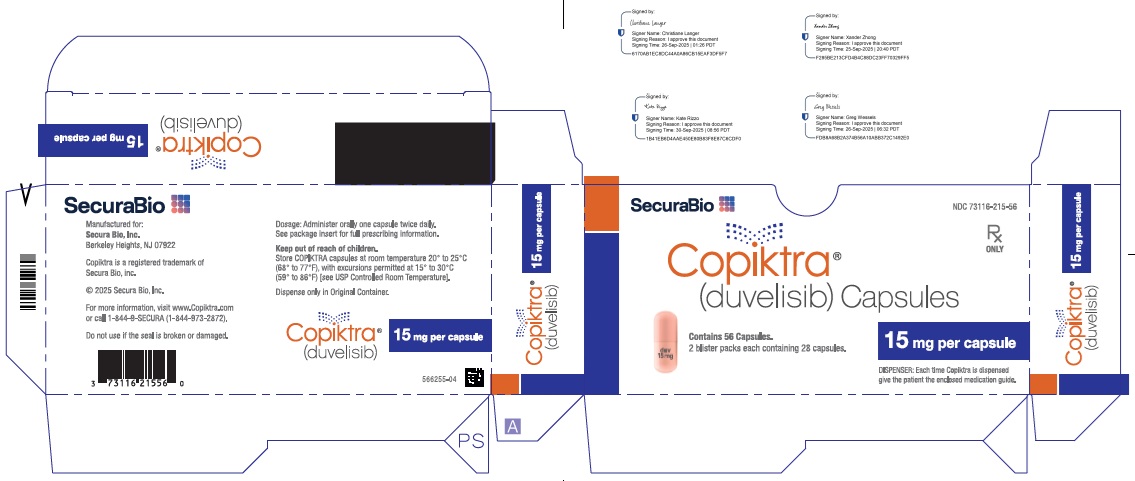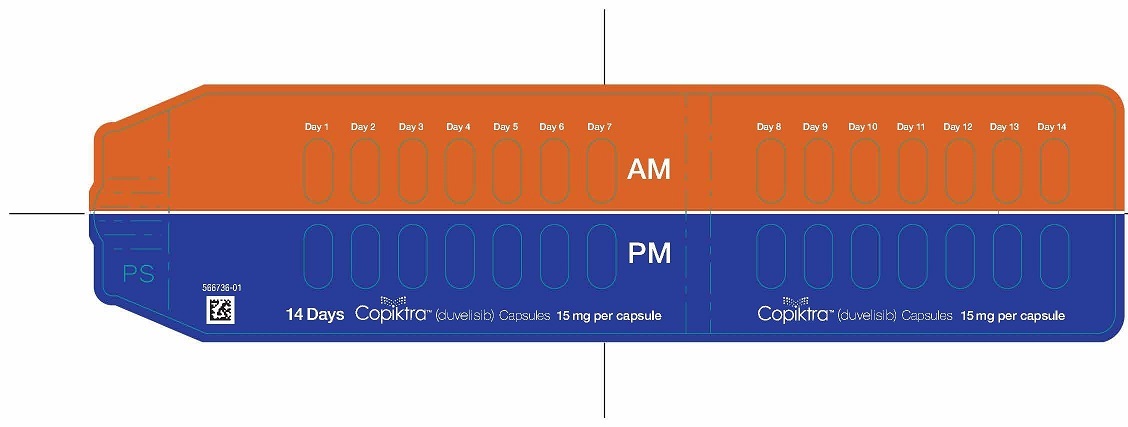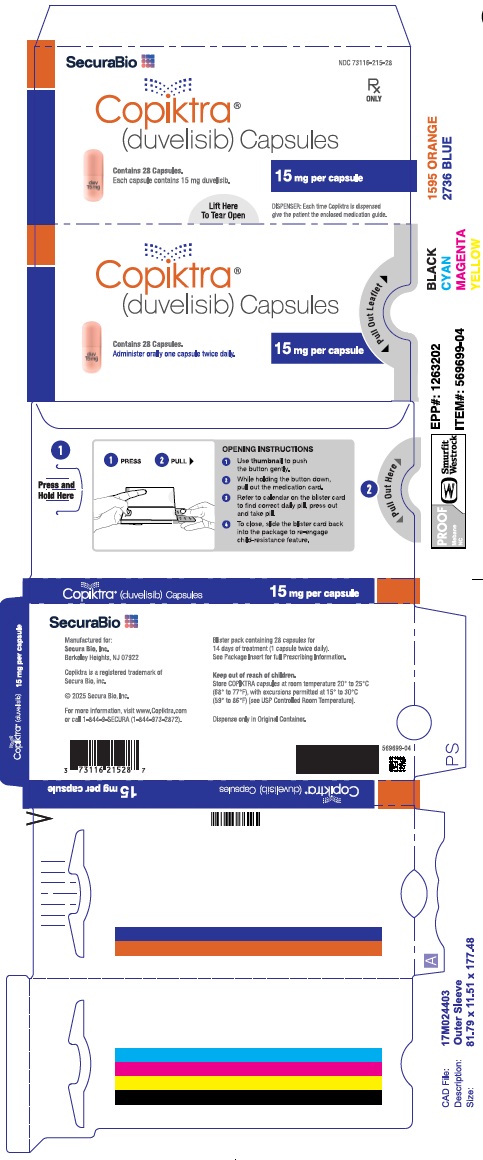 DRUG LABEL: COPIKTRA
NDC: 73116-225 | Form: CAPSULE
Manufacturer: Secura Bio, Inc
Category: prescription | Type: HUMAN PRESCRIPTION DRUG LABEL
Date: 20251218

ACTIVE INGREDIENTS: DUVELISIB 25 mg/1 1
INACTIVE INGREDIENTS: SILICON DIOXIDE; CROSPOVIDONE; MAGNESIUM STEARATE; CELLULOSE, MICROCRYSTALLINE

HIGHLIGHTS OF PRESCRIBING INFORMATION

These highlights do not include all the information needed to use COPIKTRA safely and effectively. See full prescribing information for COPIKTRA.
COPIKTRA® (duvelisib), capsules for oral use
Initial U.S. Approval: 2018

WARNING: TREATMENT-RELATED MORTALITY AND SERIOUS TOXICITIES: INFECTIONS, DIARRHEA OR COLITIS, CUTANEOUS REACTIONS, AND PNEUMONITIS

See full prescribing information for complete boxed warning

- Treatment-related mortality occurred in 15% of COPIKTRA-treated patients. (5.1)
- Fatal and/or serious infections occurred in 31% of COPIKTRA-treated patients. Monitor for signs and symptoms of infection. Withhold COPIKTRA if infection is suspected. (5.2)
- Fatal and/or serious diarrhea or colitis occurred in 18% of COPIKTRA-treated patients. Monitor for the development of severe diarrhea or colitis. Withhold COPIKTRA. (5.3)
- Fatal and/or serious cutaneous reactions occurred in 5% of COPIKTRA-treated patients. Withhold COPIKTRA. (5.4)
- Fatal and/or serious pneumonitis occurred in 5% of COPIKTRA-treated patients. Monitor for pulmonary symptoms and interstitial infiltrates. Withhold COPIKTRA. (5.5)

RECENT MAJOR CHANGES

Boxed Warning, Treatment Related Mortality added
Indications and Usage, Limitations of Use added (1)
Warnings and Precautions, Treatment Related Mortality (5.1)

7/2024
7/2024
7/2024

1 INDICATIONS AND USAGE

COPIKTRA is a kinase inhibitor indicated for the treatment of adult patients with relapsed or refractory chronic lymphocytic leukemia (CLL) or small lymphocytic lymphoma (SLL) after at least two prior lines lines of systemic therapy. (1)

Limitations of Use: COPIKTRA is not indicated or recommended for the treatment of any patients with CLL or SLL as initial or second line treatment due to an increased risk of treatment-related mortality. (1)

2 DOSAGE AND ADMINISTRATION

25 mg orally, twice daily. Modify dosage for toxicity. (2.1, 2.2)

3 DOSAGE FORMS AND STRENGTHS

Capsules: 25 mg, 15 mg. (3)

4 CONTRAINDICATIONS

None.

5 WARNINGS AND PRECAUTIONS

- Hepatotoxicity: Monitor hepatic function. (5.6)
- Neutropenia: Monitor blood counts. (5.7)
- Embryo-Fetal toxicity: COPIKTRA can cause fetal harm. Advise females of reproductive potential and males with female partners of reproductive potential of potential risk to a fetus and to use effective contraception. (5.8)

6 ADVERSE REACTIONS

The most common adverse reactions (> 20%) are diarrhea or colitis, neutropenia, rash, fatigue, pyrexia, cough, nausea, upper respiratory infection, pneumonia, musculoskeletal pain, and anemia. (6)

To report SUSPECTED ADVERSE REACTIONS, contact Secura Bio, Inc. (Secura Bio) at 1-844-973-2872, or U.S. Food and Drug Administration (FDA) at 1-800-FDA-1088 or www.fda.gov/medwatch.

7 DRUG INTERACTIONS

- CYP3A4 inhibitors: Reduce COPIKTRA dose to 15 mg twice daily when co-administered with strong CYP3A4 inhibitors. (2.4, 7.1, 12.3)
- Strong CYP3A4 inducers: Avoid coadministration. (2.5, 7.1, 12.3)
- Moderate CYP3A4 inducers: Avoid coadministration. If coadministration cannot be avoided, increase the dose of COPIKTRA. (2.5, 7.1, 12.3)
- CYP3A4 substrates: Monitor for signs of toxicities when co-administering COPIKTRA with sensitive CYP3A substrates. (7.2)

8 USE IN SPECIFIC POPULATIONS

Lactation: Advise women not to breastfeed. (8.2)

FULL PRESCRIBING INFORMATION

WARNING: TREATMENT-RELATED MORTALITY AND SERIOUS TOXICITIES: INFECTIONS, DIARRHEA OR COLITIS, CUTANEOUS REACTIONS, AND PNEUMONITIS

- Treatment-related mortality occurred in 15% of COPIKTRA-treated patients [see Warnings and Precautions (5.1)].
- Fatal and/or serious infections occurred in 31% of COPIKTRA-treated patients. Monitor for signs and symptoms of infection. Withhold COPIKTRA if infection is suspected [see Warnings and Precautions (5.2)].
- Fatal and/or serious diarrhea or colitis occurred in 18% of COPIKTRA-treated patients. Monitor for the development of severe diarrhea or colitis. Withhold COPIKTRA [see Warnings and Precautions (5.3)].
- Fatal and/or serious cutaneous reactions occurred in 5% of COPIKTRA-treated patients. Withhold COPIKTRA [see Warnings and Precautions (5.4)].
- Fatal and/or serious pneumonitis occurred in 5% of COPIKTRA-treated patients. Monitor for pulmonary symptoms and interstitial infiltrates. Withhold COPIKTRA [see Warnings and Precautions (5.5)].

1 INDICATIONS AND USAGE

COPIKTRA is indicated for the treatment of adult patients with relapsed or refractory chronic lymphocytic leukemia (CLL) or small lymphocytic lymphoma (SLL) after at least two prior lines of systemic therapy.
Limitations of Use: COPIKTRA is not indicated or recommended for the treatment of any patients with CLL or SLL as initial or second line treatment due to an increased risk of treatment-related mortality.

2 DOSAGE AND ADMINISTRATION

2.1 Recommended Dosage

The recommended dose of COPIKTRA is 25 mg administered as oral capsules twice daily (BID) with or without food. A cycle consists of 28 days. The capsules should be swallowed whole. Advise patients not to open, break, or chew the capsules.

Advise patients that if a dose is missed by fewer than 6 hours, to take the missed dose right away and take the next dose as usual. If a dose is missed by more than 6 hours, advise patients to wait and take the next dose at the usual time.

2.2 Recommended Prophylaxis

Provide prophylaxis for Pneumocystis jirovecii (PJP) during treatment with COPIKTRA. Following completion of COPIKTRA treatment, continue PJP prophylaxis until the absolute CD4+ T cell count is greater than 200 cells/µL.

Withhold COPIKTRA in patients with suspected PJP of any grade, and discontinue if PJP is confirmed.

Consider prophylactic antivirals during COPIKTRA treatment to prevent cytomegalovirus (CMV) infection including CMV reactivation.

2.3 Dosage Modifications for Adverse Reactions

Manage toxicities per Table 1 with dose reduction, treatment hold, or discontinuation of COPIKTRA.

Table 1. COPIKTRA Dose Modifications and Toxicity Management
Toxicity | Adverse Reaction Grade | Recommended Management
Nonhematologic Adverse Reactions
Infections | Grade 3 or higher infection | - Withhold COPIKTRA until resolved - Resume at the same or reduced dose (see Table 2)
Infections | Clinical CMV infection or viremia (positive PCR or antigen test) | - Withhold COPIKTRA until resolved - Resume at the same or reduced dose (see Table 2) - If COPIKTRA is resumed, monitor patients for CMV reactivation (by PCR or antigen test) at least monthly
Infections | PJP | - For suspected PJP, withhold COPIKTRA until evaluated - For confirmed PJP, discontinue COPIKTRA
Non-infectious Diarrhea or colitis | Mild/moderate diarrhea (Grade 1-2, up to 6 stools per day over baseline) and responsive to antidiarrheal agents, OR Asymptomatic (Grade 1) colitis | - No change in dose - Initiate supportive therapy with antidiarrheal agents as appropriate - Monitor at least weekly until resolved
Non-infectious Diarrhea or colitis | Mild/moderate diarrhea (Grade 1-2, up to 6 stools per day over baseline) and unresponsive to antidiarrheal agents | - Withhold COPIKTRA until resolved - Initiate supportive therapy with enteric acting steroids (e.g., budesonide) - Monitor at least weekly until resolved - Resume at a reduced dose (see Table 2)
Non-infectious Diarrhea or colitis | Abdominal pain, stool with mucus or blood, change in bowel habits, peritoneal signs, OR Severe diarrhea (Grade 3, >6 stools per day over baseline) | - Withhold COPIKTRA until resolved - Initiate supportive therapy with enteric acting steroids (e.g., budesonide) or systemic steroids - Monitor at least weekly until resolved - Resume at a reduced dose (see Table 2) - For recurrent Grade 3 diarrhea or recurrent colitis of any grade, discontinue COPIKTRA
Non-infectious Diarrhea or colitis | Life-threatening | - Discontinue COPIKTRA
Cutaneous reactions | Grade 1-2 | - No change in dose - Initiate supportive care with emollients, anti-histamines (for pruritus), or topical steroids - Monitor closely
Cutaneous reactions | Grade 3 | - Withhold COPIKTRA until resolved - Initiate supportive care with emollients, anti-histamines (for pruritus), or topical steroids - Monitor at least weekly until resolved - Resume at reduced dose (see Table 2) - If severe cutaneous reaction does not improve, worsens, or recurs, discontinue COPIKTRA
Cutaneous reactions | Life-threatening | - Discontinue COPIKTRA
Cutaneous reactions | SJS, TEN, DRESS (any grade) | - Discontinue COPIKTRA
Pneumonitis without suspected infectious cause | Moderate (Grade 2) symptomatic pneumonitis | - Withhold COPIKTRA - Treat with systemic steroid therapy - If pneumonitis recovers to Grade 0 or 1, COPIKTRA may be resumed at reduced dose (see Table 2) - If non-infectious pneumonitis recurs or patient does not respond to steroid therapy, discontinue COPIKTRA
Pneumonitis without suspected infectious cause | Severe (Grade 3) or life-threatening pneumonitis | - Discontinue COPIKTRA - Treat with systemic steroid therapy
ALT/AST elevation | 3 to 5 × upper limit of normal (ULN) (Grade 2) | - Maintain COPIKTRA dose - Monitor at least weekly until return to < 3 × ULN
ALT/AST elevation | > 5 to 20 × ULN (Grade 3) | - Withhold COPIKTRA and monitor at least weekly until return to < 3 × ULN - Resume COPIKTRA at same dose (first occurrence) or at a reduced dose for subsequent occurrence (see Table 2)
ALT/AST elevation | > 20 × ULN (Grade 4) | - Discontinue COPIKTRA
Hematologic Adverse Reactions
Neutropenia | Absolute neutrophil count (ANC) 0.5 to 1.0 Gi/L | - Maintain COPIKTRA dose - Monitor ANC at least weekly
Neutropenia | ANC less than 0.5 Gi/L | - Withhold COPIKTRA. - Monitor ANC until > 0.5 Gi/L - Resume COPIKTRA at same dose (first occurrence) or at a reduced dose for subsequent occurrence (see Table 2)
Thrombocytopenia | Platelet count 25 to < 50 Gi/L (Grade 3) with Grade 1 bleeding | - No change in dose - Monitor platelet counts at least weekly
Thrombocytopenia | Platelet count 25 to < 50 Gi/L (Grade 3) with Grade 2 bleeding or Platelet count < 25 Gi/L (Grade 4) | - Withhold COPIKTRA - Monitor platelet counts until ≥ 25 Gi/L and resolution of bleeding (if applicable) - Resume COPIKTRA at same dose (first occurrence) or resume at a reduced dose for subsequent occurrence (see Table 2)
Abbreviations: ALT = alanine aminotransferase; ANC = absolute neutrophil count; AST = aspartate aminotransferase;
CMV = cytomegalovirus; DRESS = drug reaction with eosinophilia and systemic systems; PCR = polymerase chain reaction; PJP = Pneumocystis jirovecii; pneumonia; SJS = Stevens-Johnson syndrome; TEN = toxic epidermal necrolysis; ULN = upper limit of normal

Recommended dose modification levels for COPIKTRA are presented in Table 2.

Table 2. Dose Modification Levels
Dose Level | Dose
Initial Dose | 25 mg twice daily
Dose Reduction | 15 mg twice daily
Subsequent Dose Modification | Discontinue COPIKTRA if patient is unable to tolerate 15 mg twice daily.

2.4 Dosage Modification for Concomitant Use with CYP3A4 Inhibitors

Reduce COPIKTRA dose to 15 mg twice daily when coadministered with strong CYP3A4 inhibitors (e.g., ketoconazole) [see Drug Interactions (7.1)].

2.5 Dosage Modifications for Concomitant Use with CYP3A4 Inducers

Avoid coadministration of COPIKTRA with strong CYP3A4 inducers.

Avoid coadministration of COPIKTRA with moderate CYP3A4 inducers. If coadministration with a moderate CYP3A4 inducer cannot be avoided, increase the COPIKTRA dose on Day 12 of coadministration with the moderate CYP3A4 inducer as recommended in Table 3.

Table 3. Recommended Dosage Modifications for Use with Moderate CYP3A4 Inducers
Initial COPIKTRA Dosage | Recommended COPIKTRA Dosage
25 mg orally twice daily | 40 mg orally twice daily
15 mg orally twice daily | 25 mg orally twice daily

After the inducer has been discontinued for at least 14 days, resume COPIKTRA at the dose taken prior to initiating the moderate CYP3A4 inducer [see Drug Interactions (7.1), Clinical Pharmacology (12.3)]

3 DOSAGE FORMS AND STRENGTHS

Strength | Description
25 mg | White to off-white opaque and Swedish orange opaque capsule printed in black ink with "duv 25 mg"
15 mg | Pink opaque capsule printed in black ink with "duv 15 mg"

4 CONTRAINDICATIONS

None.

5 WARNINGS AND PRECAUTIONS

5.1 Treatment-related Mortality

In a randomized controlled study in patients with relapsed or refractory CLL or SLL, treatment with COPIKTRA caused increased treatment-related mortality [see Clinical Studies (14)]. With extended follow-up with a median of 63 months, treatment-related deaths occurred in 15% (23/158) of those patients in the overall population. In the indicated patient population, patients with relapsed or refractory CLL or SLL after at least two prior lines of systemic therapy, treatment-related deaths following treatment with COPIKTRA occurred in 14% (13/93) of patients. The most common cause of the treatment-related deaths were infections, which occurred in 9% and 11% of patients with relapsed or refractory CLL following at least one or two prior systemic therapies, respectively [see Adverse Reactions (6.1)]. COPIKTRA is not indicated and is not recommended for any patients in the initial or second-line treatment setting [see Indications and Usage (1)].

5.2 Infections

Serious, including fatal (18/442; 4%), infections occurred in 31% of patients receiving COPIKTRA 25 mg BID (N = 442). The most common serious infections were pneumonia, sepsis, and lower respiratory infections. Median time to onset of any grade infection was 3 months (range: 1 day to 32 months), with 75% of cases occurring within 6 months.

Treat infections prior to initiation of COPIKTRA. Advise patients to report any new or worsening signs and symptoms of infection. For grade 3 or higher infection, withhold COPIKTRA until infection has resolved. Resume COPIKTRA at the same or reduced dose [see Dosage and Administration (2.3)].

Serious, including fatal, Pneumocystis jirovecii pneumonia (PJP) occurred in 1% of patients taking COPIKTRA. Provide prophylaxis for PJP during treatment with COPIKTRA. Following completion of COPIKTRA treatment, continue PJP prophylaxis until the absolute CD4+ T cell count is greater than 200 cells/µL. Withhold COPIKTRA in patients with suspected PJP of any grade, and permanently discontinue if PJP is confirmed.

CMV reactivation/infection occurred in 1% of patients taking COPIKTRA. Consider prophylactic antivirals during COPIKTRA treatment to prevent CMV infection including CMV reactivation. For clinical CMV infection or viremia, withhold COPIKTRA until infection or viremia resolves. If COPIKTRA is resumed, administer the same or reduced dose and monitor patients for CMV reactivation by PCR or antigen test at least monthly [see Dosage and Administration (2.3)].

5.3 Diarrhea or Colitis

Serious, including fatal (1/442; 0.2%), diarrhea or colitis occurred in 18% of patients receiving COPIKTRA 25 mg BID (N = 442). The median time to onset of any grade diarrhea or colitis was 4 months (range: 1 day to 33 months), with 75% of cases occurring by 8 months. The median event duration was 0.5 months (range: 1 day to 29 months; 75th percentile: 1 month).

Advise patients to report any new or worsening diarrhea. For non-infectious diarrhea or colitis, follow the guidelines below:

For patients presenting with mild or moderate diarrhea (Grade 1-2) (i.e., up to 6 stools per day over baseline) or asymptomatic (Grade 1) colitis, initiate supportive care with antidiarrheal agents as appropriate, continue COPIKTRA at the current dose, and monitor the patient at least weekly until the event resolves. If the diarrhea is unresponsive to antidiarrheal therapy, withhold COPIKTRA and initiate supportive therapy with enteric acting steroids (e.g., budesonide). Monitor the patient at least weekly. Upon resolution of the diarrhea, consider restarting COPIKTRA at a reduced dose.

For patients presenting with abdominal pain, stool with mucus or blood, change in bowel habits, peritoneal signs, or with severe diarrhea (Grade 3) (i.e., > 6 stools per day over baseline) withhold COPIKTRA and initiate supportive therapy with enteric acting steroids (e.g., budesonide) or systemic steroids. A diagnostic work-up to determine etiology, including colonoscopy, should be performed. Monitor at least weekly. Upon resolution of the diarrhea or colitis, restart COPIKTRA at a reduced dose. For recurrent Grade 3 diarrhea or recurrent colitis of any grade, discontinue COPIKTRA. Discontinue COPIKTRA for life-threatening diarrhea or colitis [see Dosage and Administration (2.3)].

5.4 Cutaneous Reactions

Serious, including fatal (2/442; 0.5%), cutaneous reactions occurred in 5% of patients receiving COPIKTRA 25 mg BID (N = 442). Fatal cases included drug reaction with eosinophilia and systemic symptoms (DRESS) and toxic epidermal necrolysis (TEN). Median time to onset of any grade cutaneous reaction was 3 months (range: 1 day to 29 months, 75th percentile: 6 months), with a median event duration of 1 month (range: 1 day to 37 months, 75th percentile: 2 months).

Presenting features for the serious events were primarily described as pruritic, erythematous, or maculo-papular. Less common presenting features include exanthem, desquamation, erythroderma, skin exfoliation, keratinocyte necrosis, and papular rash. Advise patients to report any new or worsening cutaneous reactions. Review all concomitant medications and discontinue any medications potentially contributing to the event. For patients presenting with mild or moderate (Grade 1-2) cutaneous reactions, continue COPIKTRA at the current dose, initiate supportive care with emollients, anti-histamines (for pruritus), or topical steroids, and monitor the patient closely. Withhold COPIKTRA for severe (Grade 3) cutaneous reaction until resolution. Initiate supportive care with steroids (topical or systemic) or anti-histamines (for pruritus). Monitor at least weekly until resolved. Upon resolution of the event, restart COPIKTRA at a reduced dose. Discontinue COPIKTRA if severe cutaneous reaction does not improve, worsens, or recurs. For life-threatening cutaneous reactions, discontinue COPIKTRA. In patients with SJS, TEN, or DRESS of any grade, discontinue COPIKTRA [see Dosage and Administration (2.3)].

5.5 Pneumonitis

Serious, including fatal (1/442; 0.2%), pneumonitis without an apparent infectious cause occurred in 5% of patients receiving COPIKTRA 25 mg BID (N = 442). Median time to onset of any grade pneumonitis was 4 months (range: 9 days to 27 months), with 75% of cases occurring within 9 months). The median event duration was 1 month, with 75% of cases resolving by 2 months.

Withhold COPIKTRA in patients who present with new or progressive pulmonary signs and symptoms such as cough, dyspnea, hypoxia, interstitial infiltrates on a radiologic exam, or a decline by more than 5% in oxygen saturation and evaluate for etiology. If the pneumonitis is infectious, patients may be restarted on COPIKTRA at the previous dose once the infection, pulmonary signs and symptoms resolve. For moderate non-infectious pneumonitis (Grade 2), treat with systemic corticosteroids, and resume COPIKTRA at a reduced dose upon resolution. If non-infectious pneumonitis recurs or does not respond to steroid therapy, discontinue COPIKTRA. For severe or life-threatening non-infectious pneumonitis, discontinue COPIKTRA and treat with systemic steroids [see Dosage and Administration (2.3)].

5.6 Hepatotoxicity

Grade 3 and 4 ALT and/or AST elevation developed in 8% and 2%, respectively, in patients receiving COPIKTRA 25 mg BID (N = 442). Two percent of patients had both an ALT or AST greater than 3 x ULN and total bilirubin greater than 2 x ULN. Median time to onset of any grade transaminase elevation was 2 months (range: 3 days to 26 months), with a median event duration of 1 month (range: 1 day to 16 months).

Monitor hepatic function during treatment with COPIKTRA. For Grade 2 ALT/AST elevation (greater than 3 to 5 × ULN), maintain COPIKTRA dose and monitor at least weekly until return to less than 3 × ULN. For Grade 3 ALT/AST elevation (greater than 5 to 20 × ULN), withhold COPIKTRA and monitor at least weekly until return to less than 3 × ULN. Resume COPIKTRA at the same dose (first occurrence) or at a reduced dose for subsequent occurrence. For grade 4 ALT/AST elevation (greater than 20 × ULN) discontinue COPIKTRA [see Dosage and Administration (2.3)].

5.7 Neutropenia

Grade 3 or 4 neutropenia occurred in 42% of patients receiving COPIKTRA 25 mg BID (N = 442), with Grade 4 neutropenia occurring in 24% of all patients. The median time to onset of Grade ≥ 3 neutropenia was 2 months (range: 3 days to 31 months), with 75% of cases occurring within 4 months.

Monitor neutrophil counts at least every 2 weeks for the first 2 months of COPIKTRA therapy, and at least weekly in patients with neutrophil counts < 1.0 Gi/L (Grade 3-4). Withhold COPIKTRA in patients presenting with neutrophil counts < 0.5 Gi/L (Grade 4). sMonitor until ANC is > 0.5 Gi/L, resume COPIKTRA at same dose for the first occurrence or a reduced dose for subsequent occurrence [see Dosage and Administration (2.3)].

5.8 Embryo-fetal Toxicity

Based on findings in animals and its mechanism of action, COPIKTRA can cause fetal harm when administered to a pregnant woman. In animal reproduction studies, administration of duvelisib to pregnant rats and rabbits during organogenesis caused adverse developmental outcomes including embryo-fetal mortality (resorptions, post-implantation loss, and decreased viable fetuses), alterations to growth (lower fetal weights) and structural abnormalities (malformations) at maternal doses approximately 10 times and 39 times the maximum recommended human dose (MRHD) of 25 mg BID in rats and rabbits, respectively. Advise pregnant women of the potential risk to a fetus. Advise females of reproductive potential and males with female partners of reproductive potential to use effective contraception during treatment and for 1 month after the last dose [see Use in Specific Populations (8.1, 8.3) and Clinical Pharmacology (12.1, 12.3)].

6 ADVERSE REACTIONS

The following adverse reactions have been associated with COPIKTRA in clinical trials and are discussed in greater detail in other sections of the prescribing information:

- Treatment-related Mortality [see Warnings and Precautions (5.1)]
- Infections [see Warnings and Precautions (5.2)]
- Diarrhea or Colitis [see Warnings and Precautions (5.3)]
- Cutaneous Reactions [see Warnings and Precautions (5.4)]
- Pneumonitis [see Warnings and Precautions (5.5)]
- Hepatotoxicity [see Warnings and Precautions (5.6)]
- Neutropenia [see Warnings and Precautions (5.7)]

6.1 Clinical Trial Experience

Because clinical trials are conducted under widely variable conditions, adverse reaction rates observed in clinical trials of a drug cannot be directly compared with rates in clinical trials of another drug and may not reflect the rates observed in practice.

Summary of Clinical Trial Experience in B-cell Malignancies

The data described below reflect exposure to COPIKTRA in two single-arm, open-label clinical trials, one open-label extension clinical trial, and one randomized, open-label, actively controlled clinical trial totaling 442 patients with previously treated hematologic malignancies primarily including CLL/SLL (69%) and FL (22%). Patients were treated with COPIKTRA 25 mg BID until unacceptable toxicity or progressive disease. The median duration of exposure was 9 months (range: 0.1 to 53 months), with 36% (160/442) of patients having at least 12 months of exposure.

For the 442 patients, the median age was 67 years (range: 30 to 90 years), 65% were male, 92% were White, and 93% had an Eastern Cooperative Oncology Group (ECOG) performance status of 0 to 1. Patients had a median of 2 prior therapies. The trials required hepatic transaminases at least ≤ 3 times upper limit of normal (ULN), total bilirubin ≤ 1.5 times ULN, and serum creatinine ≤ 1.5 times ULN. Patients were excluded for prior exposure to a PI3K inhibitor within 4 weeks.

Fatal adverse reactions within 30 days of the last dose occurred in 36 patients (8%) treated with COPIKTRA 25 mg BID.

Serious adverse reactions were reported in 289 patients (65%). The most frequent serious adverse reactions that occurred were infection (31%), diarrhea or colitis (18%), pneumonia (17%), rash (5%), and pneumonitis (5%).

Adverse reactions resulted in treatment discontinuation in 156 patients (35%), most often due to diarrhea or colitis, infection, and rash. COPIKTRA was dose reduced in 104 patients (24%) due to adverse reactions, most often due to diarrhea or colitis and transaminase elevation. The median time to first dose modification or discontinuation was 4 months (range: 0.1 to 27 months), with 75% of patients having their first dose modification or discontinuation within 7 months.

Common Adverse Reactions

Table 4 summarizes common adverse reactions in patients receiving COPIKTRA 25 mg BID, and Table 5 summarizes the treatment-emergent laboratory abnormalities. The most common adverse reactions (reported in ≥ 20% of patients) were diarrhea or colitis, neutropenia, rash, fatigue, pyrexia, cough, nausea, upper respiratory infection, pneumonia, musculoskeletal pain, and anemia.

Table 4. Common Adverse Reactions (≥ 10% Incidence) in Patients with B-cell Malignancies Receiving COPIKTRA
Adverse Reactions | COPIKTRA 25 mg BID (N = 442)
Adverse Reactions | Any Grade n (%) | Grade ≥ 3 n (%)
Blood and lymphatic system disorders
Neutropenia† Anemia† Thrombocytopenia† | 151 (34) 90 (20) 74 (17) | 132 (30) 48 (11) 46 (10)
Gastrointestinal disorders
Diarrhea or colitis† a Nausea† Abdominal pain Vomiting Mucositis Constipation | 222 (50) 104 (24) 78 (18) 69 (16) 61 (14) 57 (13) | 101 (23) 4 (< 1) 9 (2) 6 (1) 6 (1) 1 (< 1)
General disorders and administration site conditions
Fatigue† Pyrexia | 126 (29) 115 (26) | 22 (5) 7 (2)
Hepatobiliary disorders
Transaminase elevation† b | 67 (15) | 34 (8)
Infections and infestations
Upper respiratory tract infection† Pneumonia† c Lower respiratory tract infection† | 94 (21) 91 (21) 46 (10) | 2 (< 1) 67 (15) 11 (3)
Metabolism and nutrition disorders
Decreased appetite Edema† Hypokalemia† | 63 (14) 60 (14) 45 (10) | 2 (< 1) 6 (1) 17 (4)
Musculoskeletal and connective tissue disorders
Musculoskeletal pain† Arthralgia | 90 (20) 46 (10) | 6 (1) 1 (< 1)
Nervous system disorders
Headache† | 55 (12) | 1 (< 1)
Respiratory, thoracic and mediastinal disorders
Cough† Dyspnea† | 111 (25) 52 (12) | 2 (< 1) 8 (2)
Skin and subcutaneous tissue disorders
Rash†d | 136 (31) | 41 (9)
†Grouped term for reactions with multiple preferred terms
aDiarrhea or colitis includes the preferred terms: colitis, enterocolitis, colitis microscopic, colitis ulcerative, diarrhea, diarrhea hemorrhagic
bTransaminase elevation includes the preferred terms: alanine aminotransferase increased, aspartate aminotransferase increased, transaminases increased, hypertransaminasemia, hepatocellular injury, hepatotoxicity
cPneumonia includes the preferred terms: All preferred terms containing "pneumonia" except for "pneumonia aspiration"; bronchopneumonia, bronchopulmonary aspergillosis
dRash includes the preferred terms: dermatitis (including allergic, exfoliative, perivascular), erythema (including multiforme), rash (including exfoliative, erythematous, follicular, generalized, macular & papular, pruritic, pustular), toxic epidermal necrolysis and toxic skin eruption, drug reaction with eosinophilia and systemic symptoms, drug eruption, Stevens-Johnson syndrome

Grade 4 adverse reactions occurring in ≥ 2% of recipients of COPIKTRA included neutropenia (18%), thrombocytopenia (6%), sepsis (3%), hypokalemia and increased lipase (2% each), and pneumonia and pneumonitis (2% each).

Table 5. Most Common New or Worsening Laboratory Abnormalities (≥ 20% Any Grade) in Patients with B-cell Malignancies Receiving COPIKTRA
Laboratory Parameter a | COPIKTRA 25 mg BID (N = 442)
Laboratory Parameter a | Any Grade n (%)b | Grade ≥ 3 n (%)b
Hematology abnormalities
Neutropenia Anemia Thrombocytopenia Lymphocytosis Leukopenia Lymphopenia | 276 (63) 198 (45) 170 (39) 132 (30) 129 (29) 90 (21) | 184 (42) 66 (15) 65 (15) 92 (21) 34 (8) 39 (9)
Chemistry abnormalities
ALT increased AST increased Lipase increased Hypophosphatemia ALP increased Serum amylase increased Hyponatremia Hyperkalemia Hypoalbuminemia Creatinine increased Hypocalcemia | 177 (40) 163 (37) 133 (36) 136 (31) 128 (29) 101 (28) 116 (27) 114 (26) 111 (25) 106 (24) 100 (23) | 34 (8) 24 (6) 58 (16) 23 (5) 7 (2) 16 (4) 30 (7) 14 (3) 7 (2) 7 (2) 12 (3)
a Includes laboratory abnormalities that are new or worsening in grade or with worsening from baseline unknown.
b Percentages are based on number of patients with at least one post-baseline assessment; not all patients were evaluable.

Grade 4 laboratory abnormalities developing in ≥ 2% of patients included neutropenia (24%), thrombocytopenia (7%), lipase increase (4%), lymphocytopenia (3%), and leukopenia (2%).

Summary of Clinical Trial Experience in CLL/SLL

DUO Study

The safety data below reflects exposure in a randomized, open-label, actively controlled clinical trial for adult patients with CLL or SLL who received at least one prior therapy. Of 313 patients treated, 158 received COPIKTRA monotherapy and 155 received ofatumumab. The 442-patient safety analysis above includes patients from DUO [see Clinical Studies (14)].

COPIKTRA was administered at 25 mg BID in 28-day treatment cycles until unacceptable toxicity or progressive disease. The comparator group received 12 doses of ofatumumab with an initial dose of 300 mg intravenous (IV) on Day 1 followed a week later by 7 weekly doses of 2000 mg IV, followed 4 weeks later by 2000 mg IV every 4 weeks for 4 doses.

In the total study population, the median age was 69 years (range: 39 to 90 years), 60% were male, 92% were White, and 91% had an ECOG performance status of 0 to 1. Patients had a median of 2 prior therapies, with 61% of patients having received 2 or more prior therapies. The trial required a hemoglobin ≥ 8 g/dL and platelets ≥ 10,000 µL with or without transfusion support, hepatic transaminases ≤ 3 times upper limit of normal (ULN), total bilirubin ≤ 1.5 times ULN, and serum creatinine ≤ 2 times ULN. The trial excluded patients with prior autologous transplant within 6 months or allogeneic transplant, prior exposure to a PI3K inhibitor or a Bruton's tyrosine kinase (BTK) inhibitor, and uncontrolled autoimmune hemolytic anemia or idiopathic thrombocytopenic purpura. [see Clinical Studies (14)].

During randomized treatment, the median duration of exposure to COPIKTRA was 11.6 months with 72% (114/158) exposed for ≥ 6 months and 49% (77/158) exposed for ≥ 1 year. The median duration of exposure to ofatumumab was 5.3 months, with 77% (120/155) receiving at least 10 of 12 doses.

Fatal adverse reactions within 30 days of the last dose occurred in 12% (19/158) of patients treated with COPIKTRA and in 4% (7/155) of patients treated with ofatumumab.

Serious adverse reactions were reported in 73% (115/158) of patients treated with COPIKTRA and most often involved infection (38% of patients; 60/158) and diarrhea or colitis (23% of patients; 36/158).

COPIKTRA was discontinued in 57 patients (36%), most often due to diarrhea or colitis, infection, and rash. COPIKTRA was dose reduced in 46 patients (29%) due to adverse reactions, most often due to diarrhea or colitis and rash.

Common Adverse Reactions

Table 6 summarizes selected adverse reactions in Study 1, and Table 7 summarizes treatment-emergent laboratory abnormalities. The most common adverse reactions with COPIKTRA (reported in ≥ 20% of patients) were diarrhea or colitis, neutropenia, pyrexia, upper respiratory tract infection, pneumonia, rash, fatigue, nausea, anemia and cough.

Table 6. Common Nonhematologic Adverse Reactions (≥ 10% Incidence) in Patients with CLL/SLL Receiving COPIKTRA (DUO)
Adverse Reactions | COPIKTRA N = 158 |  | Ofatumumab N = 155
Adverse Reactions | Any Grade (%) | Grade ≥ 3 (%) | Any Grade (%) | Grade ≥ 3 (%)
Gastrointestinal disorders
Diarrhea or colitis† a Nausea† Constipation Abdominal pain Vomiting | 57 23 17 16 15 | 25 0 <1 3 0 | 14 11 8 7 7 | 2 0 0 0 0
General disorders and administration site conditions
Pyrexia Fatigue† | 29 25 | 3 4 | 10 23 | <1 4
Hepatobiliary disorders
Transaminase elevation†d | 11 | 6 | 4 | <1
Infections and infestations
Upper respiratory tract infection† Pneumonia†b Lower respiratory tract infection† | 28 27 18 | 0 22 4 | 16 8 10 | <1 3 1
Investigations
Weight decreased | 11 | 0 | 2 | 0
Metabolism and nutrition disorders
Decreased appetite Edema† | 13 11 | 0 1 | 3 5 | <1 0
Musculoskeletal and connective tissue disorders
Musculoskeletal pain† | 17 | 1 | 12 | <1
Respiratory, thoracic and mediastinal disorders
Cough† | 23 | 1 | 16 | 0
Dyspnea | 12 | 3 | 7 | 0
Skin and subcutaneous tissue disorders
Rash†c | 27 | 11 | 15 | <1
Grades were obtained per CTCAE version 4.03.
†Grouped term for reactions with multiple preferred terms
aDiarrhea or colitis includes the preferred terms: colitis, enterocolitis, colitis microscopic, colitis ulcerative, diarrhea
bPneumonia includes the preferred terms: All preferred term containing "pneumonia" except for "pneumonia aspiration"; bronchopneumonia, bronchopulmonary aspergillosis
cRash includes the preferred terms: dermatitis (including allergic, exfoliative, perivascular), erythema (including multiforme), rash (including exfoliative, erythematous, follicular, generalized, macular & papular, pruritic, pustular), toxic skin eruption, drug eruption
dTransaminase elevation includes the preferred terms: alanine aminotransferase increased, aspartate aminotransferase increased, transaminases increased, hepatotoxicity

Table 7. Most Common New or Worsening Laboratory Abnormalities (≥ 20% Any Grade) in Patients with CLL/SLL Receiving COPIKTRA (DUO)
Laboratory Parameter | COPIKTRA N = 158 |  | Ofatumumab N = 155
Laboratory Parameter | Any Grade (%) | Grade ≥ 3 (%) | Any Grade (%) | Grade ≥ 3 (%)
Hematology abnormalities
Neutropenia Anemia Thrombocytopenia Lymphocytosis | 67 55 43 30 | 49 20 16 22 | 52 36 34 11 | 37 7 8 6
Chemistry abnormalities
ALT increased Lipase increased AST increased Phosphate decreased Hyperkalemia Hyponatremia Amylase increased Hypoalbuminemia Creatinine increased Alkaline phosphatase increased Hypocalcemia Hypokalemia | 42 37 36 34 31 31 31 31 29 27 25 20 | 7 12 3 3 4 7 5 2 1 0 1 8 | 12 15 14 20 24 18 10 15 31 14 17 8 | 0 3 1 3 1 3 1 1 0 0 1 0
Grades were obtained per CTCAE version 4.03.

Grade 4 laboratory abnormalities that developed in ≥ 2% of COPIKTRA treated patients included neutropenia (32%), thrombocytopenia (6%), lymphopenia (3%), and hypokalemia (2%).

The data above are not an adequate basis for comparison of rates between the study drug and the active control.

Long-Term Safety Follow-Up

The comparative safety data from the 5 year follow up in those treated with either COPIKTRA (n=158) or ofatumumab (n=155) were analyzed in adult patients with CLL or SLL as part of a randomized, open-label, actively controlled clinical trial (DUO) [see Clinical Studies (14)].

Fatal adverse reactions occurred in 15% (23/158) of patients treated with COPIKTRA and in 3% (5/155) of patients treated with ofatumumab. The most common fatal adverse reactions in the COPIKTRA arm were infections and respiratory adverse reactions, occurring in 9% and 3% of patients, respectively.

7 DRUG INTERACTIONS

7.1 Effects of Other Drugs on COPIKTRA

Strong CYP3A4 Inhibitors

Coadministration with a strong CYP3A4 inhibitor increases duvelisib AUC [see Clinical Pharmacology (12.3)], which may increase the risk of COPIKTRA toxicities. Reduce COPIKTRA dosage when co-administered with a strong CYP3A4 inhibitor [see Dosage and Administration (2.4)].

Strong and Moderate CYP3A4 Inducers

Coadministration with a strong or moderate CYP3A4 inducer decreases duvelisib area under the curve (AUC) [see Clinical Pharmacology (12.3)], which may reduce COPIKTRA efficacy. Avoid coadministration of strong or moderate CYP3A4 inducers with COPIKTRA. If coadministration with a moderate CYP3A4 inducer cannot be avoided, increase the COPIKTRA dose. [see Dosage and Administration (2.5), Clinical Pharmacology (12.3)].

7.2 Effects of COPIKTRA on Other Drugs

CYP3A4 Substrates

Coadministration with COPIKTRA increases AUC of a sensitive CYP3A4 substrate [see Clinical Pharmacology (12.3)] which may increase the risk of toxicities of these drugs. Consider reducing the dose of the sensitive CYP3A4 substrate and monitor for signs of toxicities of the co-administered sensitive CYP3A4 substrate.

8 USE IN SPECIFIC POPULATIONS

8.1 Pregnancy

Risk Summary

Based on findings from animal studies and the mechanism of action, COPIKTRA can cause fetal harm when administered to a pregnant woman [see Clinical Pharmacology (12.1)].

There are no available data in pregnant women to inform the drug-associated risk. In animal reproduction studies, administration of duvelisib to pregnant rats and rabbits during organogenesis caused adverse developmental outcomes including embryo-fetal mortality (resorptions, post-implantation loss, and decreased viable fetuses), alterations to growth (lower fetal weights) and structural abnormalities (malformations) at maternal doses 10 times and 39 times the MRHD of 25 mg BID in rats and rabbits, respectively (see Data).

The estimated background risk of major birth defects and miscarriage for the indicated population is unknown. All pregnancies have a background risk of birth defect, loss, or other adverse outcomes. In the U.S. general population, the estimated background risk of major birth defects and miscarriage in clinically recognized pregnancies is 2 to 4% and 15 to 20%, respectively.

Data

Animal Data

In an embryo-fetal development study in rats, pregnant animals received daily oral doses of duvelisib of 0, 10, 50, 150 and 275 mg/kg/day during the period of organogenesis. Administration of duvelisib at doses ≥ 50 mg/kg/day resulted in adverse developmental outcomes including reduced fetal weights and external abnormalities (bent tail and fetal anasarca), and doses ≥ 150 mg/kg/day resulted in maternal toxicity including mortality and no live fetuses (100% resorption) in surviving dams. In another study in pregnant rats receiving oral doses of duvelisib up to 35 mg/kg/day during the period of organogenesis, no maternal or embryo-fetal effects were observed. The dose of 50 mg/kg/day in rats is approximately 10 -times the MRHD of 25 mg BID.

In an embryo-fetal development study in rabbits, pregnant animals received daily oral doses of duvelisib of 0, 25, 100, and 200 mg/kg/day during the period of organogenesis. Administration of duvelisib at doses ≥ 100 mg/kg/day resulted in maternal toxicity (body weight losses or lower mean body weights and increased mortality) and adverse developmental outcomes (increased resorptions and post-implantation loss, abortion, and decreased numbers of viable fetuses). In another study in pregnant rabbits receiving oral doses of duvelisib up to 75 mg/kg/day, no maternal or embryo-fetal effects were observed. The dose of 100 mg/kg/day in rabbits is approximately 39 times the MRHD of 25 mg BID.

8.2 Lactation

Risk Summary

There are no data on the presence of duvelisib and/or its metabolites in human milk, the effects on the breastfed child, or on milk production. Because of the potential for serious adverse reactions from duvelisib in a breastfed child, advise lactating women not to breastfeed while taking COPIKTRA and for 1 month after the last dose.

8.3 Females and Males of Reproductive Potential

COPIKTRA can cause fetal harm when administered to a pregnant woman [see Use in Specific Populations (8.1)].

Pregnancy Testing

Conduct pregnancy testing before initiation of COPIKTRA treatment.

Contraception

Females

Based on animal studies, COPIKTRA can cause fetal harm when administered to a pregnant woman. Advise females of reproductive potential to use effective contraception during treatment with COPIKTRA and for 1 month after the last dose.

Males

Advise male patients with female partners of reproductive potential to use effective contraception during treatment with COPIKTRA and for 1 month after the last dose.

Infertility

Based on testicular findings in animals, male fertility may be impaired by treatment with COPIKTRA [see Nonclinical Toxicology (13.1)]. There are no data on the effect of COPIKTRA on human fertility.

8.4 Pediatric Use

Safety and effectiveness of COPIKTRA have not been established in pediatric patients. Pediatric studies have not been conducted.

8.5 Geriatric Use

Clinical trials of COPIKTRA included 270 patients (61%) that were 65 years of age and older and 104 (24%) that were 75 years of age and older. No major differences in efficacy or safety were observed between patients less than 65 years of age and patients 65 years of age and older.

11 DESCRIPTION

COPIKTRA (duvelisib) is a kinase inhibitor.

Duvelisib is a white-to-off-white crystalline solid with the empirical formula C22H17ClN6O•H2O and a molecular weight of 434.88 g/mol. Hydration can vary with relative humidity. Duvelisib contains a single chiral center as (S) enantiomer. Duvelisib is soluble in ethanol and practically insoluble in water. Duvelisib is described chemically as a hydrate of (S)-3-(1-(9H-purin-6-ylamino)ethyl)-8-chloro-2-phenylisoquinolin-1(2H)-one and has the following chemical structure:

COPIKTRA capsules are for oral administration and are supplied as white to off-white opaque and Swedish orange opaque capsules (25 mg, on anhydrous basis) or pink opaque capsules (15 mg, on anhydrous basis), and contain the following inactive ingredients: colloidal silicon dioxide, crospovidone, magnesium stearate, and microcrystalline cellulose. Capsule shells contain gelatin, titanium dioxide, black ink, and red iron oxide.

12 CLINICAL PHARMACOLOGY

12.1 Mechanism of Action

Duvelisib is an inhibitor of PI3K with inhibitory activity predominantly against PI3K-δ and PI3K-γ isoforms expressed in normal and malignant B-cells. Duvelisib induced growth inhibition and reduced viability in cell lines derived from malignant B-cells and in primary CLL tumor cells. Duvelisib inhibits several key cell-signaling pathways, including B-cell receptor signaling and CXCR12-mediated chemotaxis of malignant B-cells. Additionally, duvelisib inhibits CXCL12-induced T cell migration and M-CSF and IL-4 driven M2 polarization of macrophages.

12.2 Pharmacodynamics

At the recommended dose of 25 mg BID, reductions in levels of phosphorylated AKT (a downstream marker for PI3K inhibition) were observed in patients treated with COPIKTRA.

Cardiac Electrophysiology

The effect of multiple doses of COPIKTRA 25 and 75 mg BID on the QTc interval was evaluated in patients with previously treated hematologic malignancies. Increases of > 20 ms in the QTc interval were not observed.

12.3 Pharmacokinetics

Duvelisib exposure increased in a dose-proportional manner over a dose range of 8 mg to 75 mg twice daily (0.3 to 3 times the recommended dosage).

At steady state following 25 mg BID administration of duvelisib in patients, the geometric mean (CV%) maximum concentration (Cmax) was 1.5 (64%) µg/mL and AUC was 7.9 (77%) µg•h/mL.

Absorption

The absolute bioavailability of 25 mg duvelisib after a single oral dose in healthy volunteers was 42%. The median time to peak concentration (Tmax) was observed at 1 to 2 hours in patients.

Effect of Food

COPIKTRA may be administered without regard to food. The administration of a single dose of COPIKTRA with a high-fat meal (fat accounted for approximately 50% of the total caloric content of the meal) decreased Cmax by approximately 37% and decreased the AUC by approximately 6%, relative to fasting conditions.

Distribution

Protein binding of duvelisib is greater than 98% with no concentration dependence. The mean blood-to-plasma ratio was 0.5. The geometric mean (CV%) apparent volume of distribution at steady state (Vss/F) is 28.5 L (62%). Duvelisib is a substrate of P-glycoprotein (P-gp) and BCRP in vitro.

Elimination

The geometric mean (CV%) apparent systemic clearance at steady-state is 4.2 L/hr (56%) in patients with lymphoma or leukemia. The geometric mean (CV%) terminal elimination half-life of duvelisib is 4.7 hours (57%).

Metabolism

Duvelisib is primarily metabolized by cytochrome P450 CYP3A4.

Excretion

Following a single 25 mg oral dose of radiolabeled duvelisib, 79% of the radioactivity was excreted in feces (11% unchanged) and 14% was excreted in the urine (< 1% unchanged).

Specific Populations

Age (18 to 90 years), sex, race, renal impairment (creatinine clearance 23 to 80 mL/ min), hepatic impairment (Child Pugh Class A, B, and C) and body weight (40 to 154 kg) had no clinically significant effect on the exposure of duvelisib.

Drug Interaction Studies

CYP3A4 Inhibitors

Coadministration of a single COPIKTRA 10 mg dose with ketoconazole (strong CYP3A4 inhibitor) at 200 mg BID for 5 days in healthy adults increased duvelisib Cmax by 1.7-fold and AUC by 4-fold. Based on physiologically-based pharmacokinetic (PBPK) modeling and simulation, the increase in duvelisib exposure at steady state is estimated to be ~2-fold when coadministered with strong CYP3A4 inhibitors [see Dosage and Administration (2.4) and Drug Interactions (7.1)]. PBPK modeling and simulation estimated no effect on duvelisib exposures from concomitantly used mild or moderate CYP3A4 inhibitors.

Strong and Moderate CYP3A4 Inducers

Coadministration of a single COPIKTRA 25 mg dose with rifampin (strong CYP3A4 inducer) 600 mg once daily for 7 days in healthy adults decreased duvelisib Cmax by 66% and AUC by 82% [see Dosage and Administration (2.5) and Drug Interactions (7.1)].

Co-administration of etravirine (moderate CYP3A4 inducer) 200 mg twice daily of etravirine for 12 days with a single COPIKTRA 25 mg dose in healthy adults decreased duvelisib Cmax by 16% and AUC by 35%. [see Dosage and Administration (2.5) and Drug Interactions (7.1)].

CYP3A4 Substrates

Coadministration of multiple doses of COPIKTRA 25 mg BID for 5 days with a single midazolam (sensitive CYP3A4 substrate) 2 mg dose in healthy adults increased the midazolam AUC by 4.3-fold and Cmax by 2.2-fold [see Drug Interactions (7.2)].

In Vitro Studies

Duvelisib is a substrate of P-glycoprotein (P-gp) and breast cancer-resistant protein (BCRP).

Duvelisib does not inhibit OAT1, OAT3, OCT1, OCT2, OATP1B1, OATP1B3, BCRP, or P-gp.

13 NONCLINICAL TOXICOLOGY

13.1 Carcinogenesis, Mutagenesis, Impairment of Fertility

Carcinogenicity studies have not been conducted with duvelisib.

Duvelisib did not cause genetic damage in in vitro or in vivo assays.

Fertility studies with duvelisib were not conducted. Histological findings in male and female rats were observed in the repeat dose toxicity studies and included testis (seminiferous epithelial atrophy, decreased weight, soft testes), and epididymis (small size, oligo/aspermia) in males and ovary (decreased weight) and uterus (atrophy) in females.

14 CLINICAL STUDIES

DUO Study

A randomized, multicenter, open-label trial (DUO Study; NCT02004522) compared COPIKTRA versus ofatumumab in 319 adult patients with CLL (N = 312) or SLL (N = 7) after at least one prior therapy. The trial excluded patients with prior autologous transplant within 6 months or allogeneic transplant, prior exposure to a PI3K inhibitor or a Bruton's tyrosine kinase (BTK) inhibitor. The trial required hepatic transaminases ≤ 3 times upper limit of normal (ULN), total bilirubin ≤ 1.5 times ULN, and serum creatinine ≤ 2 times ULN.

The study randomized patients with a 1:1 ratio to receive either COPIKTRA 25 mg BID until disease progression or unacceptable toxicity or ofatumumab for 7 cycles. Ofatumumab was administered intravenously at an initial dose of 300 mg, followed one week later by 2000 mg once weekly for 7 doses, and then 2000 mg once every 4 weeks for 4 additional doses.

The approval of COPIKTRA was based on efficacy and safety analysis of patients with at least 2 prior lines of therapy, where the benefit:risk appeared greater in this more heavily pretreated population compared to the overall trial population.

In this subset (95 randomized to COPIKTRA, 101 to ofatumumab), the median patient age was 69 years (range: 40 to 90 years), 59% were male, and 88% had an ECOG performance status of 0 or 1. Forty-six percent received 2 prior lines of therapy, and 54% received 3 or more prior lines. At baseline, 52% of patients had at least one tumor ≥ 5 cm, and 22% of patients had a documented 17p deletion.

During randomized treatment, the median duration of exposure to COPIKTRA was 13 months (range: 0.2 to 37), with 80% of patients receiving at least 6 months and 52% receiving at least 12 months of COPIKTRA. The median duration of exposure to ofatumumab was 5 months (range: < 0.1 to 6).

Efficacy was based on progression-free survival (PFS) as assessed by an Independent Review Committee (IRC). Other efficacy measures included overall response rate. Efficacy of COPIKTRA compared to ofatumumab specifically in patients treated with at least two prior therapies is presented in Table 8 and Figure 1.

Table 8. Efficacy in CLL or SLL After at Least Two Prior Therapies (DUO)
Outcome per IRC | COPIKTRA N = 95 | Ofatumumab N = 101
PFS
Number of events, n (%) | 55 (58) | 70 (69)
Progressive disease | 44 | 62
Death | 11 | 8
Median PFS (SE), months a | 16.4 (2.1) | 9.1 (0.5)
Hazard Ratio (SE), b COPIKTRA/ofatumumab | 0.40 (0.2)
Response rate
ORR, n (%)c | 74 (78) | 39 (39)
CR | 0 (0) | 0 (0)
PR | 74 (78) | 39 (39)
Difference in ORR, % (SE) | 39 (6.4)
Abbreviations: CI = confidence interval; CR = complete response; IRC = Independent Review Committee; PFS = progression-free survival; PR = partial response; SE = standard error
a Kaplan-Meier estimate
b Standard Error of ln(hazard ratio) = 0.2
c IWCLL or revised IWG response criteria, with modification for treatment-related lymphocytosis

Figure 1. Kaplan-Meier Curve of PFS per IRC In Patients with at Least 2 Prior Therapies (DUO)

Increased Mortality in Patients with Relapsed or Refractory CLL or SLL Treated with COPIKTRA

Final overall survival (OS) analysis was conducted with a median follow-up time of 63 months. Fifty percent (80/160) of patients in the overall population died in the COPIKTRA arm, and 44% (70/159) of patients died in the ofatumumab arm. Treatment of patients in the overall population with duvelisib compared with ofatumumab demonstrated an OS HR of 1.09 (95% CI: 0.79, 1.51) with a median OS of 52 months (95% CI: 42, 68) in those patients treated with COPIKTRA and a median OS of 63 months (95% CI: 41 mo, NE) in those treated with ofatumumab. In the indicated population, those patients with relapsed or refractory CLL or SLL after at least 2 prior lines of systemic therapy, 56% (53/95) of patients died in the COPIKTRA arm and 49% (49/101) of patients died in the ofatumumab arm. Treatment of patients in the indicated population with duvelisib compared with ofatumumab demonstrated an OS HR of 1.06 (95% CI: 0.71, 1.58) with a median OS of 44 months (95% CI: 32, 57) in those patients treated with COPIKTRA and a median OS of 47 months (95% CI: 29,75) in those treated with ofatumumab.

16 HOW SUPPLIED/STORAGE AND HANDLING

COPIKTRA (duvelisib) capsules are supplied as follows:

Capsule Strength | Description | Package Configuration | NDC No
25 mg | White to off-white and Swedish orange opaque capsules marked with "duv 25 mg" in black ink | - 14-day (28ct) single blister pack - 28-day (56ct) carton (2 × 28ct blister packs per carton) | - 73116-225-28 - 73116-225-56
15 mg | Pink opaque capsules marked with "duv 15 mg" in black ink | - 14-day (28ct) single blister pack - 28-day (56ct) carton (2 × 28ct blister packs per carton) | - 73116-215-28 - 73116-215-56
Abbreviations: HDPE = high-density polyethylene; NDC = National Drug Code; No. = number

Store at 20° to 25°C (68° to 77°F), with excursions permitted at 15° to 30°C (59° to 86°F) [see USP Controlled Room Temperature]. Retain in original package until dispensing. Dispense blister packs in original container.

17 PATIENT COUNSELING INFORMATION

Advise the patient to read the FDA-approved patient labeling (Medication Guide).

Physicians and healthcare professionals are advised to discuss the following with patients prior to treatment with COPIKTRA:

● Treatment-related Mortality

Advise patients that COPIKTRA has been associated with increased deaths due to side effects of therapy in a randomized study when compared to standard therapy. The main reason for death was infection [see Warnings and Precautions (5.1)].

Infections

Advise patients that COPIKTRA can cause serious infections that may be fatal. Advise patients to immediately report symptoms of infection (e.g., fever, chills) [see Warnings and Precautions (5.2)].

● Diarrhea or Colitis

Advise patients that COPIKTRA can cause serious diarrhea or colitis (inflammation of the gut) that may be fatal, and to notify their healthcare provider immediately about any new or worsening diarrhea, stool with mucus or blood, or abdominal pain [see Warnings and Precautions (5.3)].

● Cutaneous Reactions

Advise patients that COPIKTRA can cause a serious skin rash that may be fatal, and to notify their healthcare provider immediately if they develop a new or worsening skin rash [see Warnings and Precautions (5.4)].

● Pneumonitis

Advise patients that COPIKTRA may cause pneumonitis (inflammation of the lungs) that may be fatal, and to report any new or worsening respiratory symptoms including cough or difficulty breathing [see Warnings and Precautions (5.5)].

● Hepatotoxicity

Advise patients that COPIKTRA may cause significant elevations in liver enzymes, and that monitoring of liver tests is needed. Advise patients to report symptoms of liver dysfunction including jaundice (yellow eyes or yellow skin), abdominal pain, bruising, or bleeding [see Warnings and Precautions (5.6)].

● Neutropenia

Advise patients of the need for periodic monitoring of blood counts. Advise patients to notify their healthcare provider immediately if they develop a fever or any sign of infection [see Warnings and Precautions (5.7)].

● Embryo-Fetal Toxicity

Advise females to inform their healthcare provider if they are pregnant or become pregnant. Inform female patients of the risk to a fetus [see Use in Specific Populations (8.1)].

Advise females of reproductive potential to use effective contraception during treatment and for 1 month after receiving the last dose of COPIKTRA [see Warnings and Precautions (5.8) and Use in Specific Populations (8.1, 8.3)].

Advise males with female partners of reproductive potential to use effective contraception during treatment with COPIKTRA and for 1 month after the last dose [see Warnings and Precautions (5.8) and Use in Specific Populations (8.1, 8.3)].

● Lactation

Advise lactating women not to breastfeed during treatment with COPIKTRA and for 1 month after the last dose [see Use in Specific Populations (8.2)].

● Instructions for Taking COPIKTRA

Advise patients to take COPIKTRA exactly as prescribed. COPIKTRA may be taken with or without food; the capsules should be swallowed whole [see Dosage and Administration (2.1)].

Advise patients that if a dose is missed by fewer than 6 hours, to take the missed dose right away and take the next dose as usual. If a dose is missed by more than 6 hours, advise patients to wait and take the next dose at the usual time [see Dosage and Administration (2.3)].

Advise patients to inform their healthcare providers of all concomitant medications, including prescription medicines, over-the-counter drugs, vitamins, and herbal products, before and during treatment with COPIKTRA [see Drug Interactions (7)].

Distributed by:

Secura Bio, Inc.

200 Connell Drive, Suite 1100

Berkeley Heights, NJ 07922

© Secura Bio

USCPR250042-1

MEDICATION GUIDE
COPIKTRA™ (co-PIK-trah)
(duvelisib)
capsules

What is the most important information I should know about COPIKTRA?
COPIKTRA can cause serious side effects, including:

- Death due to treatment side effects. COPIKTRA can cause severe, life-threatening side effects that can lead to death. The serious side effects are listed below. Infections were the most common cause of death. If you develop any of these or any new or worsening side effects, tell your healthcare provider right away.
- Infections . Infections are common during COPIKTRA treatment, and can be serious and can lead to death. Tell your healthcare provider right away if you have a fever, chills, or other signs of an infection during treatment with COPIKTRA.
- Diarrhea or inflammation of your intestine. Diarrhea or inflammation of your intestine (colitis) is common during COPIKTRA treatment, and can be serious and can lead to death. Your healthcare provider may prescribe an anti-diarrhea medicine for your diarrhea. Tell your healthcare provider right away if you have any new or worsening diarrhea, stool with mucus or blood, or if you have severe stomach-area (abdominal) pain. Your healthcare provider should prescribe medicine to help your diarrhea and check you at least weekly. If your diarrhea is severe or anti-diarrhea medicines did not work, you may need treatment with a steroid medicine.
- Skin reactions. Rashes are common with COPIKTRA treatment. COPIKTRA can cause rashes and other skin reactions that can be serious and can lead to death. Tell your healthcare provider right away if you get a new or worsening skin rash, or other skin reactions during treatment with COPIKTRA, including:
  - painful sores or ulcers on your skin, lips, or in your mouth
  - severe rash with blisters or peeling skin
  - rash with itching
  - rash with fever

Your healthcare provider may need to prescribe medicines, including a steroid medicine, to help treat your skin rash or other skin reactions.

- Inflammation of the lungs . COPIKTRA can cause inflammation of your lungs which can be serious and can lead to death. Tell your healthcare provider right away if you get new or worsening cough or difficulty breathing. Your healthcare provider may do tests to check your lungs if you have breathing problems during treatment with COPIKTRA. Your healthcare provider may treat you with a steroid medicine if you develop inflammation of the lungs that is not due to an infection.

If you have any of the above serious side effects during treatment with COPIKTRA, your healthcare provider may stop your treatment for a period of time, change your dose of COPIKTRA, or completely stop your treatment with COPIKTRA.
See "What are the possible side effects of COPIKTRA?" " for more information about side effects.

What is COPIKTRA?
COPIKTRA is a prescription medicine used to treat adults with:

- Chronic lymphocytic leukemia (CLL) or small lymphocytic lymphoma (SLL) who have received at least 2 prior therapies and they did not work or are no longer working.

COPIKTRA should not be used as the first or second medicine to treat anyone, including people with CLL or SLL because of an increased risk of death due to treatment side effects.
It is not known if COPIKTRA is safe and effective in children less than 18 years of age.

What should I tell my healthcare provider before taking COPIKTRA?
Before taking COPIKTRA, tell your healthcare provider about all of your medical conditions, including if you:

- have intestinal problems
- have lung or breathing problems
- have an infection
- are pregnant or plan to become pregnant. COPIKTRA can harm your unborn baby.
  - Your healthcare provider should do a pregnancy test to see if you are pregnant before you start treatment with COPIKTRA.
  - Females who are able to become pregnant should use effective birth control (contraception) during treatment with COPIKTRA and for at least 1 month after the last dose of COPIKTRA. Talk to your healthcare provider about birth control methods that may be right for you. Tell your healthcare provider right away if you become pregnant or think you are pregnant during treatment with COPIKTRA.
  - Males with female partners who are able to become pregnant should use effective birth control (contraception) during treatment with COPIKTRA and for at least 1 month after the last dose of COPIKTRA.

- are breastfeeding or plan to breastfeed. It is not known if COPIKTRA passes into breast milk. Do not breastfeed during treatment and for at least 1 month after the last dose of COPIKTRA.

Tell your healthcare provider about all the medicines you take, including prescription and over-the-counter medicines, vitamins, and herbal supplements. COPIKTRA and certain other medicines may affect each other.

How should I take COPIKTRA?

- Take COPIKTRA exactly the way your healthcare provider tells you.
- Your healthcare provider may change your dose of COPIKTRA or tell you to stop taking COPIKTRA. Do not change your dose or stop taking COPIKTRA without talking to your healthcare provider first.
- Swallow COPIKTRA capsules whole.
- Do not open, break, or chew COPIKTRA capsules.
- You may take COPIKTRA with or without food.
- Do not miss a dose of COPIKTRA. If you miss a dose of COPIKTRA by less than 6 hours , take the missed dose right away, and then take the next dose at your usual time. If you miss a dose by more than 6 hours , wait and take the next dose at your usual time.
- If you take too much COPIKTRA, call your healthcare provider right away or go to the nearest hospital emergency room.

What are possible side effects of COPIKTRA?
COPIKTRA may cause serious side effects, including:

- See "WHAT IS THE MOST IMPORTANT INFORMATION I SHOULD KNOW ABOUT COPIKTRA?"
- Elevated liver enzymes. COPIKTRA may cause abnormalities in liver blood tests. Your healthcare provider should do blood tests during your treatment with COPIKTRA to check for liver problems. Tell your healthcare provider right away if you get any symptoms of liver problems, including yellowing of your skin or the white part of your eyes (jaundice), pain in the stomach (abdominal) region, bruising or bleeding more easily than normal.
- Low white blood cell count (neutropenia). Neutropenia is common with COPIKTRA treatment and can sometimes be serious. Your healthcare provider should check your blood counts regularly during treatment with COPIKTRA. Tell your healthcare provider right away if you have a fever or any signs of infection during treatment with COPIKTRA.

The most Common side effects of COPIKTRA include:

- tiredness
- fever
- cough

- nausea
- upper respiratory infection
- bone and muscle pain
- low red blood cell count

These are not all the possible side effects of COPIKTRA.
Call your doctor for medical advice about side effects. You may report side effects to FDA at 1-800-FDA-1088.

How should I store COPIKTRA?

- Store COPIKTRA at room temperature between 68°F to 77°F (20°C to 25°C).
- Keep COPIKTRA in its original container until you are ready to take your dose.

Keep COPIKTRA and all medicines out of the reach of children.

General information about the safe and effective use of COPIKTRA:
Medicines are sometimes prescribed for purposes other than those listed in a Medication Guide. Do not use COPIKTRA for a condition for which it was not prescribed. Do not give COPIKTRA to other people, even if they have the same symptoms that you have. It may harm them. You can ask your pharmacist or healthcare provider for information about COPIKTRA that is written for health professionals.

What are the ingredients in COPIKTRA?
Active ingredient: duvelisib
Inactive ingredients: Colloidal silicon dioxide, crospovidone, magnesium stearate, and microcrystalline cellulose. Capsule shells contain gelatin, titanium dioxide, black ink, and red iron oxide.
Distributed by: Secura Bio, Inc. 1995 Village Center Circle, Suite 128, Las Vegas, NV 89134
© Secura Bio
USCPR2419201
For more information , go to www.Copiktra.com or call on 1-844-9-SECURA (1-844-973-2872)

This Medication Guide has been approved by the U.S. Food and Drug Administration. Revised: 7/2024